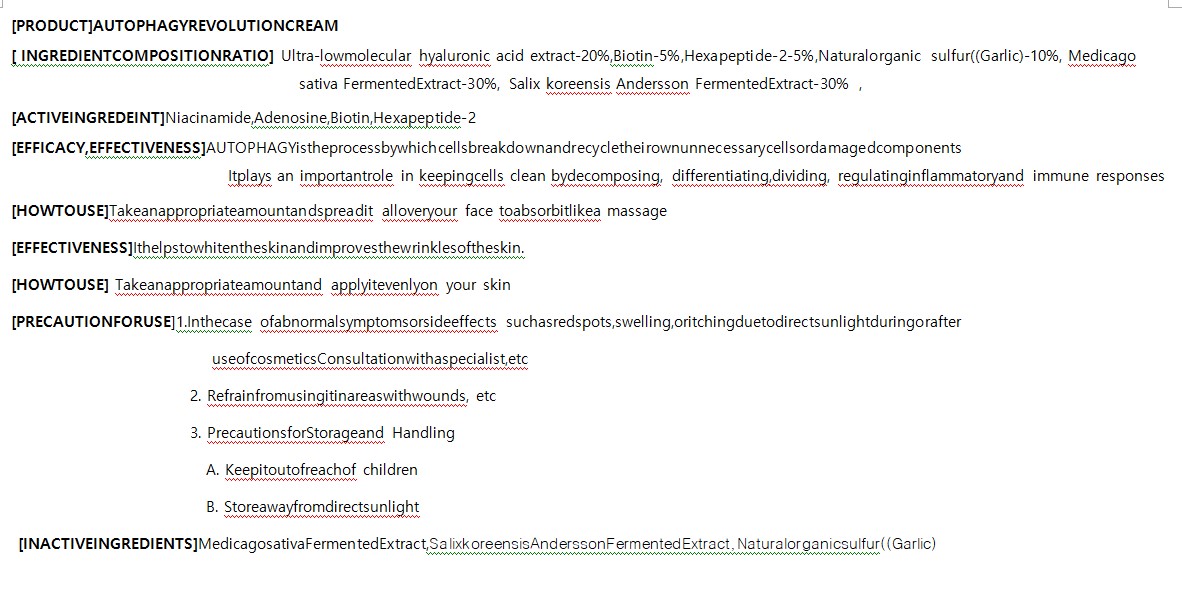 DRUG LABEL: AUTOPHAGY REVOLUTIONCREAM
NDC: 82237-0005 | Form: CREAM
Manufacturer: NFC LIFE SCIENCE CO.,LTD
Category: otc | Type: HUMAN OTC DRUG LABEL
Date: 20240222

ACTIVE INGREDIENTS: NIACINAMIDE 0.04 g/100 mL
INACTIVE INGREDIENTS: WATER

ACTIVE INGREDIENT

Niacinamide,Adenosine,Biotin,Hexapeptide-2

INACTIVE INGREDIENT

Ultra-lowmolecular hyaluronic acid extract-20%,Biotin-5%,Hexapeptide-2-5%,Naturalorganic sulfur((Garlic)-10%, Medicago sativa FermentedExtract-30%, Salix koreensis Andersson FermentedExtract-30%

PURPOSE

AUTOPHAGY is the process by which cells break down and recycle the irownun necessary cells or damaged components

Itplays an importantrole in keepingcells clean bydecomposing, differentiating,dividing, regulatinginflammatoryand immune responses

Keep out of reach of the children

INDICATIONS AND USAGE

Take an appropriate amount and apply it evenly on your skin

WARNINGS

1.In the case of abnormal symptoms or sid eeffects suchasredspots,swelling,oritchingduetodirectsunlightduringorafter

useofcosmeticsConsultationwithaspecialist,etc

Refrainfromusingitinareaswithwounds, etc

PrecautionsforStorageand Handling

Keepitoutofreachof children
Storeawayfromdirectsunlight

DOSAGE AND ADMINISTRATION

for external use only